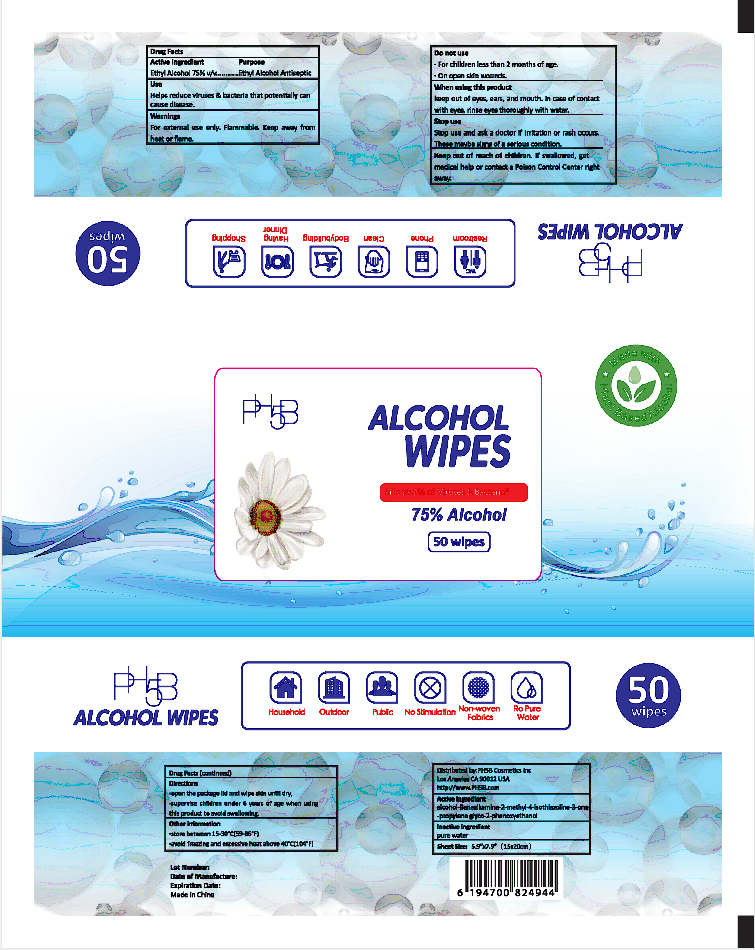 DRUG LABEL: Alcohol disinfectant wipes
NDC: 41546-016 | Form: CLOTH
Manufacturer: Zhejiang Huanghua Biological Technology Co., Ltd
Category: otc | Type: HUMAN OTC DRUG LABEL
Date: 20201207

ACTIVE INGREDIENTS: ALCOHOL 160 mL/50 1; BENZALKONIUM CHLORIDE 0.5 g/50 1; METHYLISOTHIAZOLINONE 0.5 g/50 1; PROPYLENE GLYCOL 0.5 g/50 1; PHENOXYETHANOL 0.5 g/50 1
INACTIVE INGREDIENTS: WATER

DOSAGE AND ADMINISTRATION

store between 15-30°C(59-86°F)
avoid freezing and excessive heat above 40°C(104°F)

INACTIVE INGREDIENT

pure water

INDICATIONS AND USAGE

open the package lid and wipe skin until dry.

ACTIVE INGREDIENT

alcohol

Benzalkamine

2-methyl-4-isothiazoline-3-one

propylene glyco

2-phenoxyethanol

DO NOT USE

For children less than 2 months of age.

On open skin wounds.

Keep out of reach of children. If swallowed, get medical help or contact a Poison Control Center right away.

PURPOSE

Disinfection
Sterilization
No Rinseing

Stop use and ask a doctor if irritation or rash occurs.These maybe signs of a serious condition.

WARNINGS

For external use only. Flammable. Keep away from heat or flame.